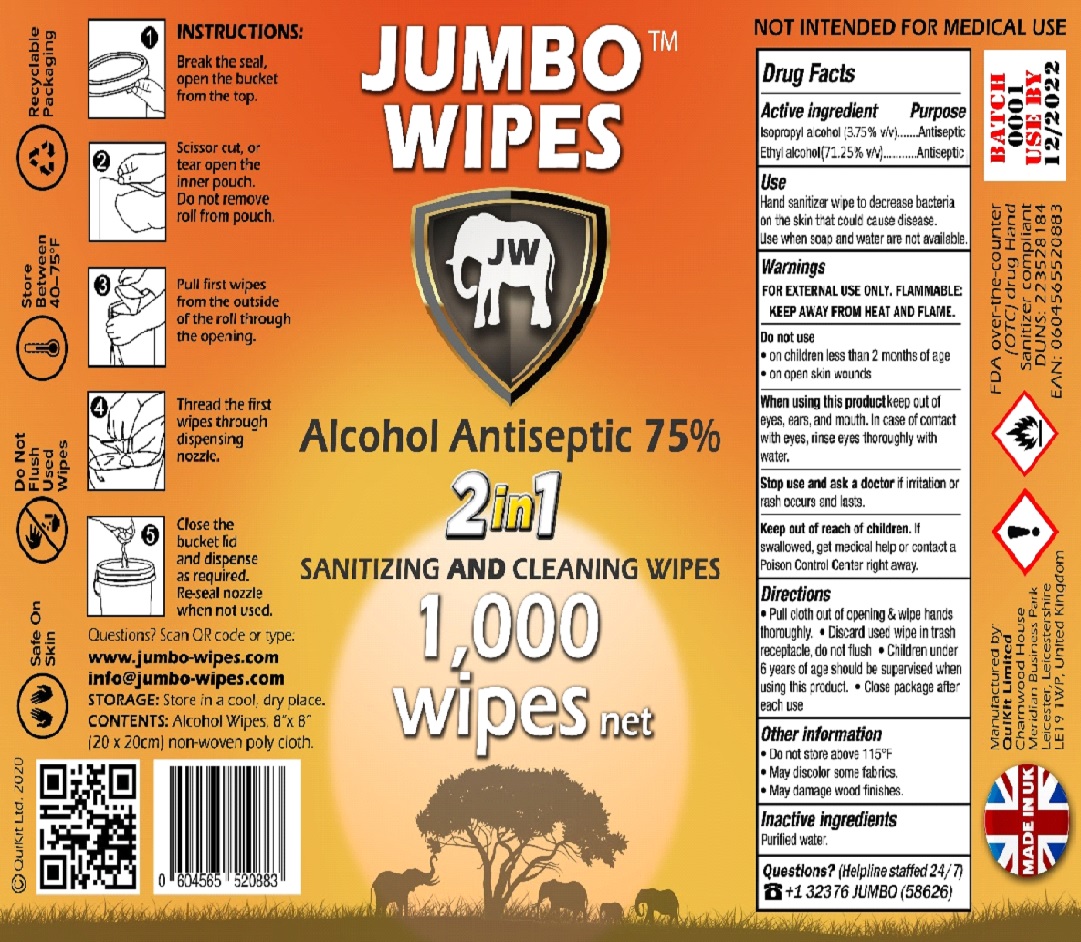 DRUG LABEL: Jumbo Wipes
NDC: 81071-001 | Form: CLOTH
Manufacturer: QUIKIT LIMITED
Category: otc | Type: HUMAN OTC DRUG LABEL
Date: 20201112

ACTIVE INGREDIENTS: ALCOHOL 71.25 mL/100 mL; ISOPROPYL ALCOHOL 3.75 mL/100 mL
INACTIVE INGREDIENTS: WATER

Jumbo-Wipes, sanitizing and cleaning wipes.

Active Ingredient

Isopropyl alcohol 3.75%

Ethyl alcohol 71.25%

Purpose

Antiseptic.

Warnings

For external use only. Flammable, keep away from heat or flame.

Do not use

• in children less than 2 months of age
• on open skin wounds

When using this product keep out of eyes, ears, and mouth. In case of contact with eyes, rinse eyes thoroughly with water.

Stop use and ask a doctor if irritation or rash occurs.

Uses

Hand sanitiser wipe to decrease bacteria on the skin that could cause disease.

Use when soap and water are not available.

Directions

- Pull cloth our of opening & wipe hands thoroughly.
- Discard used wipe in trash receptacle, do not flush.
- Children under 6 years of age should be supervised when using this product.
- Close package after each us.

Keep out of reach of children.

If swallowed, get medical help or contact a Poison Control Center right away.

Other information

Do not store above 115°F

May discolor some fabrics

May damage wood finishes

Inactive Ingredients

Purified Water